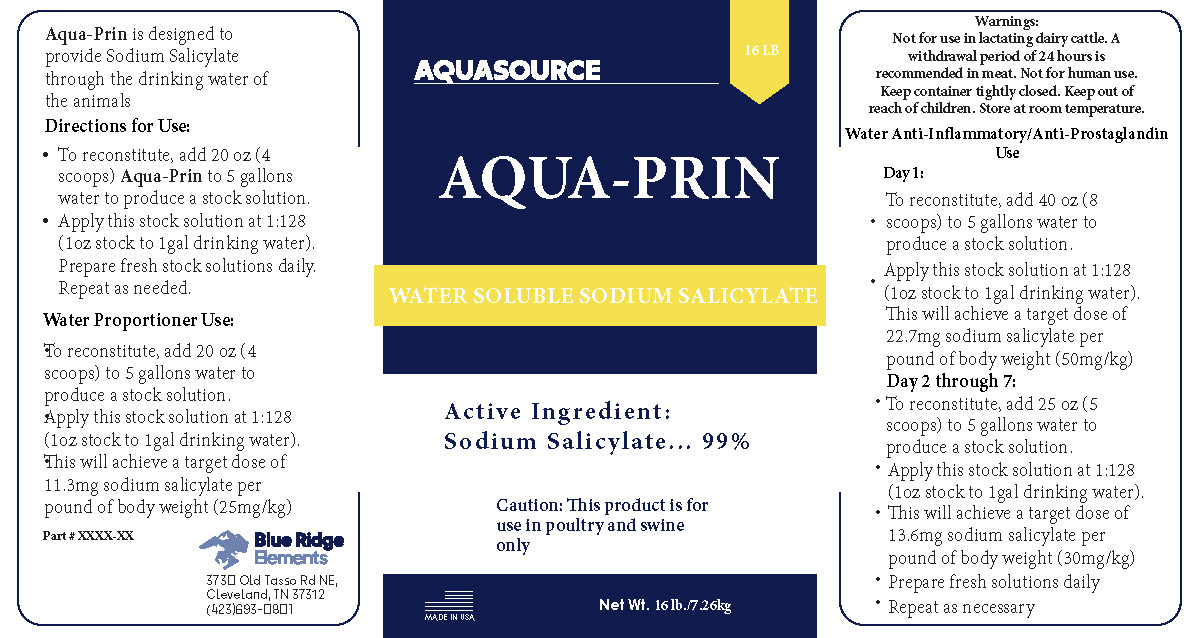 DRUG LABEL: Aquasource Aqua-Prin Water Soluble Sodium Salicylate
NDC: 86050-2990 | Form: POWDER
Manufacturer: Blendpack, Inc.
Category: animal | Type: OTC ANIMAL DRUG LABEL
Date: 20250205

ACTIVE INGREDIENTS: SODIUM SALICYLATE .99 kg/1 kg

Aquasource Aqua-Prin Water Soluble Sodium Salicylate

Aqua-Prin is designed to provide Sodium Salicylate through the drinking water of the animals

Directions for Use:

- To reconstitute, add 20 oz (4 scoops) Aqua-Prin to 5 gallons water to produce a stock solution.
- Apply this stock solution at 1:128 (1 oz stock to 1gal drinking water).
- Prepare fresh stock solutions daily. Repeat as needed.

Water Proportioner Use:

To reconstitute, add 20 oz (4 scoops) to 5 gallons water to produce a stock solution.

Apply this stock solution at 1:128 (1 oz stock to 1 gal drinking water). This will achieve a target dose of 11.3 mg sodium salicylate per pound of body weight (25mg/kg).

Warnings:

Not for use in lactating dairy cattle. A withdrawal period of 24 hours is recommended in meat. Not for human use. Keep container tightly closed. Keep out of reach of children. Store at room temperature.

Water Anti-Inflammatory/Anti-Prostaglandin Use

Day 1:

- To reconstitute, add 40 oz (8 scoops) to 5 gallons water to produce a stock solution.
- Apply this stock solution at 1:128 (1 oz stock to 1 gal drinking water). This will achieve a target dose of 22.7mg sodium salicylate per pound of body weight (50mg/kg).

Day 2 through 7:

- To reconstitute, add 25 oz (5 scoops) to 5 gallons water to produce a stock solution.
- Apply this stock solution at 1:128 (1 oz stock to 1 gal drinking water).
- This will achieve a target dose of 13.6 mg sodium salicylate per pound of body weight (30mg/kg)
- Prepare fresh solutions daily
- Repeat as necessary

PACKAGE LABEL

Add image transcription here...